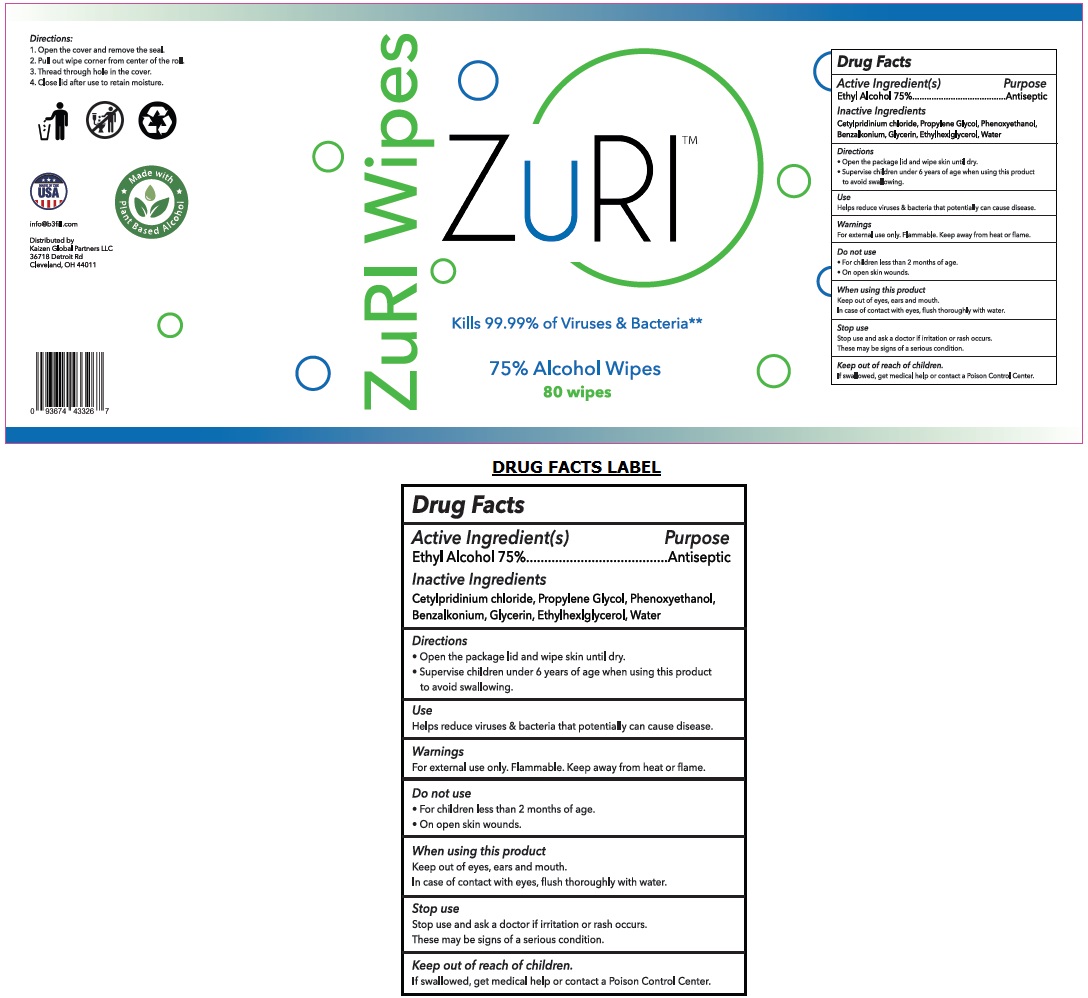 DRUG LABEL: ZuRI 75% Alcohol Wipes
NDC: 80347-075 | Form: CLOTH
Manufacturer: Kaizen Global Partners Llc
Category: otc | Type: HUMAN OTC DRUG LABEL
Date: 20201201

ACTIVE INGREDIENTS: ALCOHOL 75 mL/100 g
INACTIVE INGREDIENTS: CETYLPYRIDINIUM CHLORIDE; PROPYLENE GLYCOL; PHENOXYETHANOL; BENZALKONIUM; GLYCERIN; ETHYLHEXYLGLYCERIN; WATER

ZuRITM 75% Alcohol Wipes

Active Ingredient(s)

Ethyl Alcohol 75%

Purpose

Antiseptic

Inactive Ingredients

Cetylpyridinium chloride, Propylene Glycol, Phenoxyethanol, Benzalkonium, Glycerin, Ethylhexylglycerol, Water

Directions

• Open the package lid and wipe skin until dry.
• Supervise children under 6 years of age when using this product to avoid swallowing.

Use

Helps reduce viruses & bacteria that potentially can cause disease.

Warnings

For external use only. Flammable. Keep away from heat or flame.

Do not use

• For children less than 2 months of age
• On open skin wounds.

When using this product

Keep out of eyes, ears, and mouth.

In case of contact with eyes, flush thoroughly with water.

Stop use

Stop use and ask a doctor if irritation or rash occurs.

These maybe signs of a serious condition.

Keep out of reach of children.

If swallowed, get medical help or contact a Poison Control Center.

Kills 99.99% of Viruses & Bacteria**

Directions:

1. Open the cover and remove the seal.

2. Pull out wipe corner from center of the roll.

3. Thread through hole in the cover.

4. Close lid after use to retain moisture

MADE IN THE USA

Made with Plant Based Alcohol

info@b3fill.com

Distributed by

Kaizen Global Partners LLC

36718 Detroit Rd

Cleveland, OH 44011